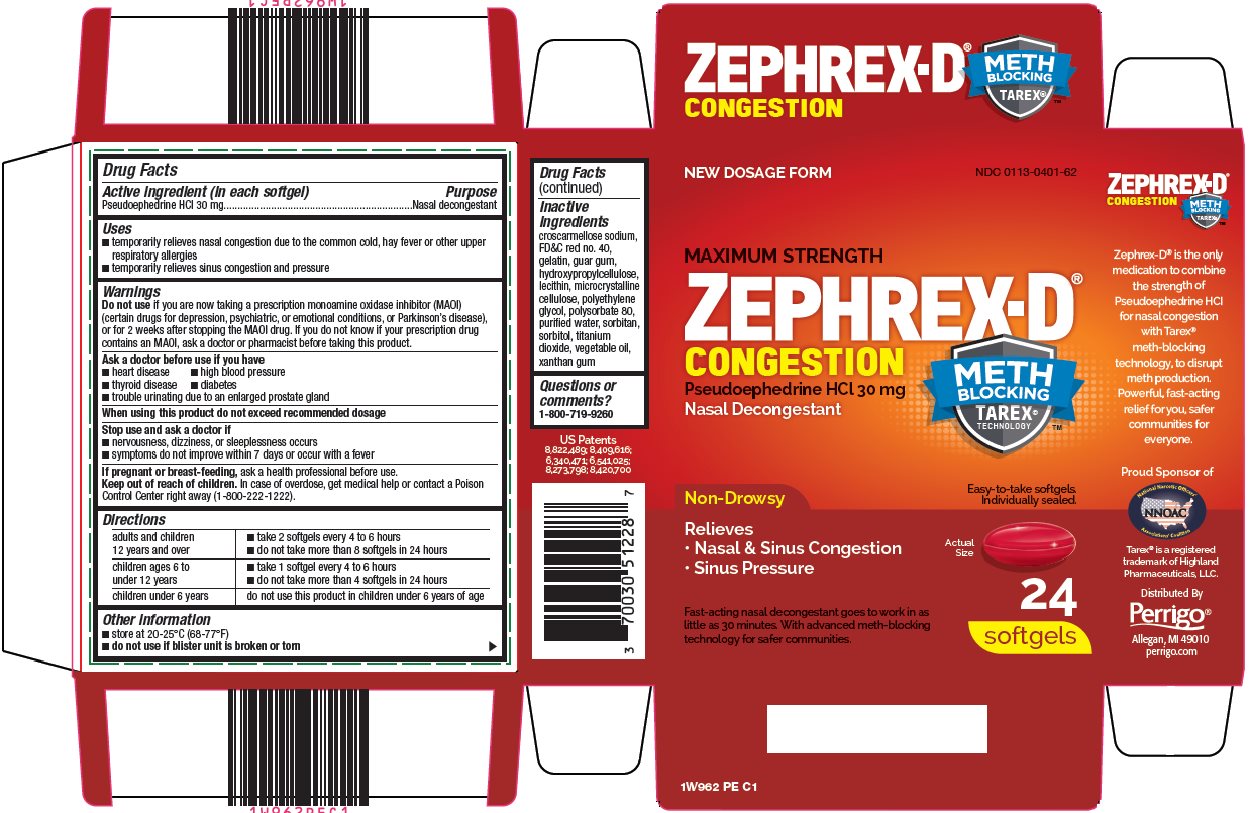 DRUG LABEL: Zephrex D
NDC: 0113-0401 | Form: CAPSULE, GELATIN COATED
Manufacturer: L. Perrigo Company
Category: otc | Type: HUMAN OTC DRUG LABEL
Date: 20241111

ACTIVE INGREDIENTS: PSEUDOEPHEDRINE HYDROCHLORIDE 30 mg/1 1
INACTIVE INGREDIENTS: CROSCARMELLOSE SODIUM; FD&C RED NO. 40; GELATIN, UNSPECIFIED; GUAR GUM; HYDROXYPROPYL CELLULOSE (1600000 WAMW); MICROCRYSTALLINE CELLULOSE; POLYETHYLENE GLYCOL, UNSPECIFIED; POLYSORBATE 80; WATER; SORBITAN; SORBITOL; TITANIUM DIOXIDE; XANTHAN GUM

Zephrex D Drug Facts

Active ingredient (in each softgel)

Pseudoephedrine HCl 30 mg

Purpose

Nasal decongestant

Uses

- temporarily relieves nasal congestion due to the common cold, hay fever or other upper respiratory allergies
- temporarily relieves sinus congestion and pressure

Warnings

Do not use

if you are now taking a prescription monoamine oxidase inhibitor (MAOI) (certain drugs for depression, psychiatric, or emotional conditions, or Parkinson’s disease), or for 2 weeks after stopping the MAOI drug. If you do not know if your prescription drug contains an MAOI, ask a doctor or pharmacist before taking this product.

Ask a doctor before use if you have

- heart disease
- high blood pressure
- thyroid disease
- diabetes
- trouble urinating due to an enlarged prostate gland

When using this product

do not exceed recommended dosage

Stop use and ask a doctor if

- nervousness, dizziness, or sleeplessness occurs
- symptoms do not improve within 7 days or occur with a fever

If pregnant or breast-feeding,

ask a health professional before use.

Keep out of reach of children.

In case of overdose, get medical help or contact a Poison Control Center right away (1-800-222-1222).

Directions

adults and children 12 years and over | - take 2 softgels every 4 to 6 hours - do not take more than 8 softgels in 24 hours
children ages 6 to under 12 years | - take 1 softgel every 4 to 6 hours - do not take more than 4 softgels in 24 hours
children under 6 years | do not use this product in children under 6 years of age

Other information

- store at 20-25°C (68-77°F)
- do not use if blister unit is broken or torn

Inactive ingredients

croscarmellose sodium, FD&C red no. 40, gelatin, guar gum, hydroxypropylcellulose, lecithin, microcrystalline cellulose, polyethylene glycol, polysorbate 80, purified water, sorbitan, sorbitol, titanium dioxide, vegetable oil, xanthan gum

Questions or comments?

1-800-719-9260

Package/Label Principal Display Panel

NEW DOSAGE FORM

MAXIMUM STRENGTH

ZEPHREX-D ®

CONGESTION

Pseudoephedrine HCl 30 mg

Nasal Decongestant

METH BLOCKING TAREX® TECHNOLOGY ™

Non-Drowsy

Relieves

Nasal & Sinus Congestion

Sinus Pressure

Easy-to-take softgels.

Individually sealed.

Actual Size

Fast-acting nasal decongestant goes to work in as little as 30 minutes. With advanced meth-blocking technology for safer communities.

24 softgels